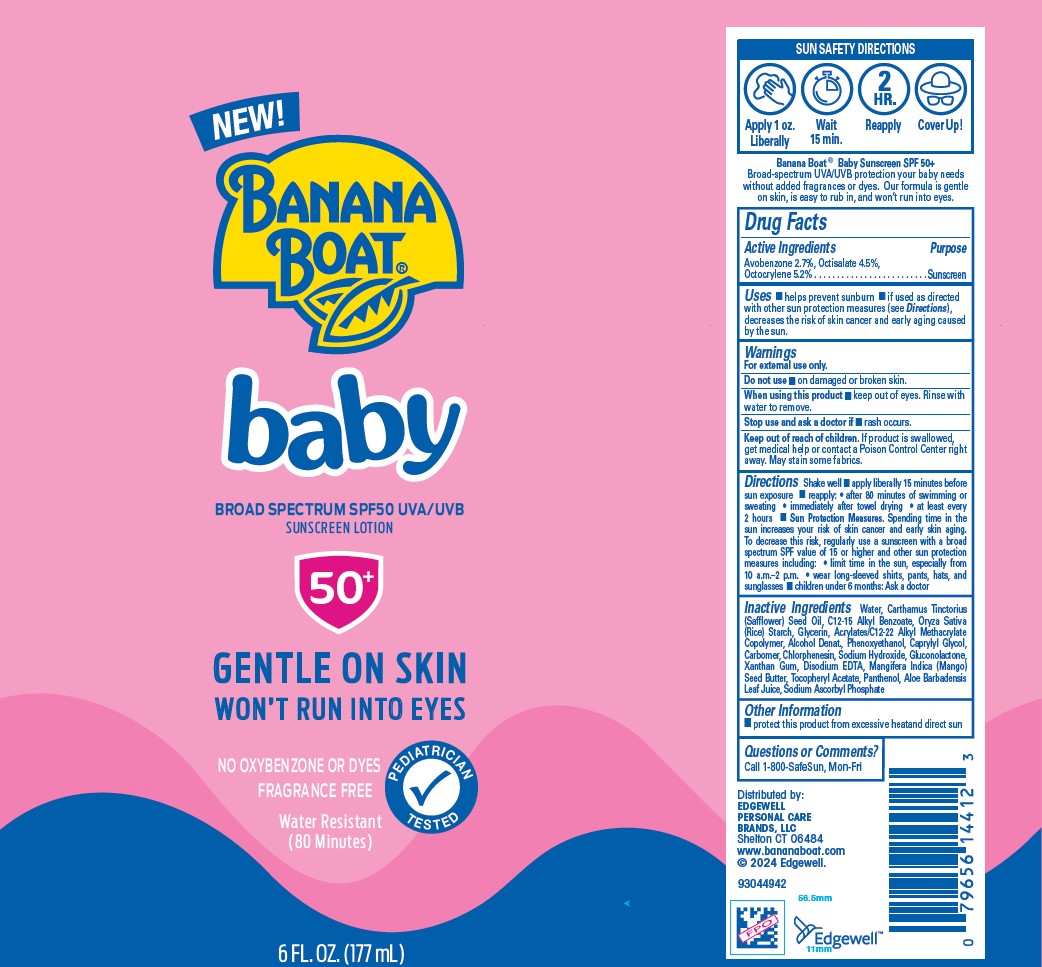 DRUG LABEL: BANANA BOAT
NDC: 63354-851 | Form: LOTION
Manufacturer: Edgewell Personal Care Brands LLC
Category: otc | Type: HUMAN OTC DRUG LABEL
Date: 20241210

ACTIVE INGREDIENTS: OCTOCRYLENE 5.2 g/100 g; AVOBENZONE 2.7 g/100 g; OCTISALATE 4.5 g/100 g
INACTIVE INGREDIENTS: WATER; .ALPHA.-TOCOPHEROL ACETATE; GLYCERIN; MANGIFERA INDICA (MANGO) SEED BUTTER; SODIUM ASCORBYL PHOSPHATE; PANTHENOL; PHENOXYETHANOL; CAPRYLYL GLYCOL; ORYZA SATIVA (RICE) STARCH; XANTHAN GUM; CARTHAMUS TINCTORIUS (SAFFLOWER) SEED OIL; CARBOMER; CHLORPHENESIN; ALKYL (C12-15) BENZOATE; ALOE BARBADENSIS LEAF JUICE; EDETATE DISODIUM; ALCOHOL; SODIUM HYDROXIDE; GLUCONOLACTONE

Active Ingredients

Avobenzone 2.7%, Octisalate 4.5%, Octocrylene 5.2%

Purpose

Sunscreen

Uses

• helps prevent sunburn • if used as directed with other sun protection measures (see Directions), decreases the risk of skin cancer and early aging caused by the sun.

Warnings

For external use only.
May stain some fabrics.

Do not use

• on damaged or broken skin.

When using this product

• keep out of eyes. Rinse with water to remove.

Stop use and ask a doctor if

• rash occurs.

Keep out of reach of children.

If product is swallowed, get medical help or contact a Poison Control Center right away.

Directions

Shake well • apply liberally 15 minutes before sun exposure • reapply: • after 80 minutes of swimming or sweating • immediately after towel drying • at least every 2 hours • Sun Protection Measures. Spending time in the sun increases your risk of skin cancer and early skin aging.To decrease this risk, regularly use a sunscreen with a broad spectrum SPF value of 15 or higher and other sun protection measures including: • limit time in the sun, especially from 10 a.m.–2 p.m. • wear long-sleeved shirts, pants, hats, and sunglasses • children under 6 months: Ask a doctor

Inactive Ingredients

Water, Carthamus Tinctorius (Safflower) Seed Oil, C12-15 Alkyl Benzoate, Oryza Sativa (Rice) Starch, Glycerin, Acrylates/C12-22 Alkyl Methacrylate Copolymer, Alcohol Denat., Phenoxyethanol, Caprylyl Glycol, Carbomer, Chlorphenesin, Sodium Hydroxide, Gluconolactone, Xanthan Gum, Disodium EDTA, Mangifera Indica (Mango) Seed Butter, Tocopheryl Acetate, Panthenol, Aloe Barbadensis Leaf Juice, Sodium Ascorbyl Phosphate

Other Information

• protect this product from excessive heatand direct sun

Questions or Comments?

Call 1-800-SafeSun, Mon-Fri

Package Display Panel

NEW!

BANANA BOAT

baby

BROAD SPECTRUM SPF50 UVA/UVB

SUNSCREEN LOTION

50+

GENTLE ON SKIN

WON'T RUN INTO EYES

NO OXYBENZONE OR DYES

FRAGRANCE FREE

PEDIATRICIAN TESTED

WATER RESISTANT

(80 MINUTES)

6 FL.OZ. (177mL)